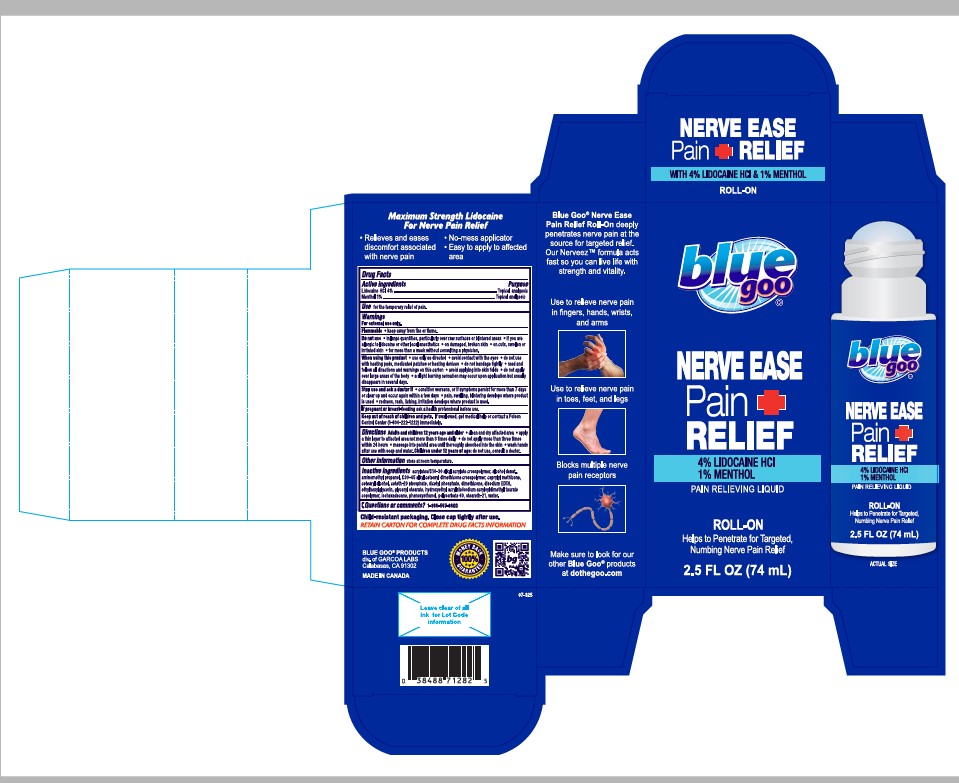 DRUG LABEL: blue goo NERVE EASE Pain RELIEF
NDC: 67385-825 | Form: LIQUID
Manufacturer: Garcoa, Inc.
Category: otc | Type: HUMAN OTC DRUG LABEL
Date: 20250910

ACTIVE INGREDIENTS: LIDOCAINE 40 mg/1 mL; MENTHOL 10 mg/1 mL
INACTIVE INGREDIENTS: ACRYLATES/C10-30 ALKYL ACRYLATE CROSSPOLYMER (60000 MPA.S AT 0.5%); ALCOHOL; AMINOMETHYL PROPANOL; C30-45 ALKYL CETEARYL DIMETHICONE CROSSPOLYMER; CAPRYLYL METHICONE; CETEARYL ALCOHOL; CETETH-20 PHOSPHATE; DICETYL PHOSPHATE; DIMETHICONE; EDETATE DISODIUM; ETHYLHEXYLGLYCERIN; GLYCERYL STEARATE; HYDROXYETHYL ACRYLATE/SODIUM ACRYLOYLDIMETHYL TAURATE COPOLYMER (100000 MPA.S AT 1.5%); ISOHEXADECANE; PHENOXYETHANOL; POLYSORBATE 60; STEARETH-21; WATER

blue goo NERVE Pain RELIEF PAIN RELIEVING LIQUID

Active ingredient(s)

Lidocaine HCl 4%

Menthol 1%

Purpose

Topical analgesic

Topical analgesic

Use(s)

Use for the temporary relief of pain.

Warnings

For External use only.

Do not use • in large quantities, particularly over raw surfaces or blistered areas • if you are allergic to lidocaine or other local anesthetics • on damages, broken skin • on cuts, swollen or irritated skin • for more than a week without consulting a physician.

When using this product • use only as directed • avoid contact with the eyes • do not use with heating pads, medicated patches or heating devices • do not bandage tightly • read and follow all directions and warnings on this carton • avoid applying into skin folds •do not apply over large areas of the body • a slight burning sensation may occur upon application but usually disappears in several days.

Stop use and ask a doctor if • condition worsens, or if symptoms persist for more than 7 days or clear up and occur again within a few days • pain, swelling, blistering develops where product is used • redness, rash, itching, irritation develops where product is used.

Flammable • keep away from fire or flame.

If pregnant or breast-feeding ask a health professional before use.

Keep out of reach of children and pets. if swallowed, get medical help or contact a Poison Control Center (1-800-222-1222) immediately.

Directions

Directions Adults and children 12 years age and older • clean and dry affected area •apply a thin layer to affected area not more than 3 times daily • do not apply more than three times within 24 hours • massage into painful area until thoroughly absorbed into the skin • wash hands after use with soap and water. Children under 12 years of age: do not use, consult a doctor.

Inactive ingredients

Inactive ingredients acrylates/Cl10-30 alkyl acrylate crosspolymer, alcohol denat.,
aminomethyl propanol, C30-45 alkyl cetearyl dimethicone crosspolymer, caprylyl methicone,
cetearyl alcohol, ceteth-20 phosphate, dicetyl phosphate, dimethicone, disodium EDTA,
ethylhexylglycerin, glyceryl stearate, hydroxyethyl acrylate/sodium acryloyldimethyl taurate
copolymer, isohexadecane, phenoxyethanol, polysorbate 60, steareth-21, water.

Questions

Question or comments? 1866-567-8600

BLUE GOO PRODUCTS

div. of GARCOA LABS

Calabasas, CA 91302

Principal Display Panel

blue goo

NERVE EASE

Pain

RELIEF

4% LIDOCAINE HCl

1% MENTHOL

PAIN RELIEVING LIQUID

ROLL-ON

Helps to Penetrate for Targeted,

Numbing Nerve Pain Relief

2.5 FL OZ (74mL)